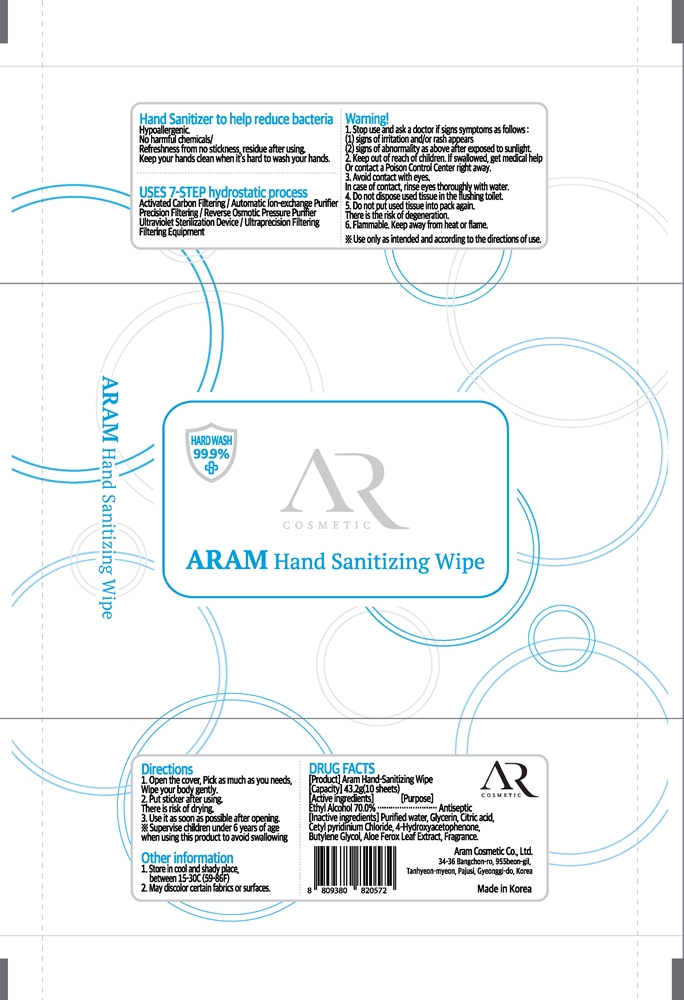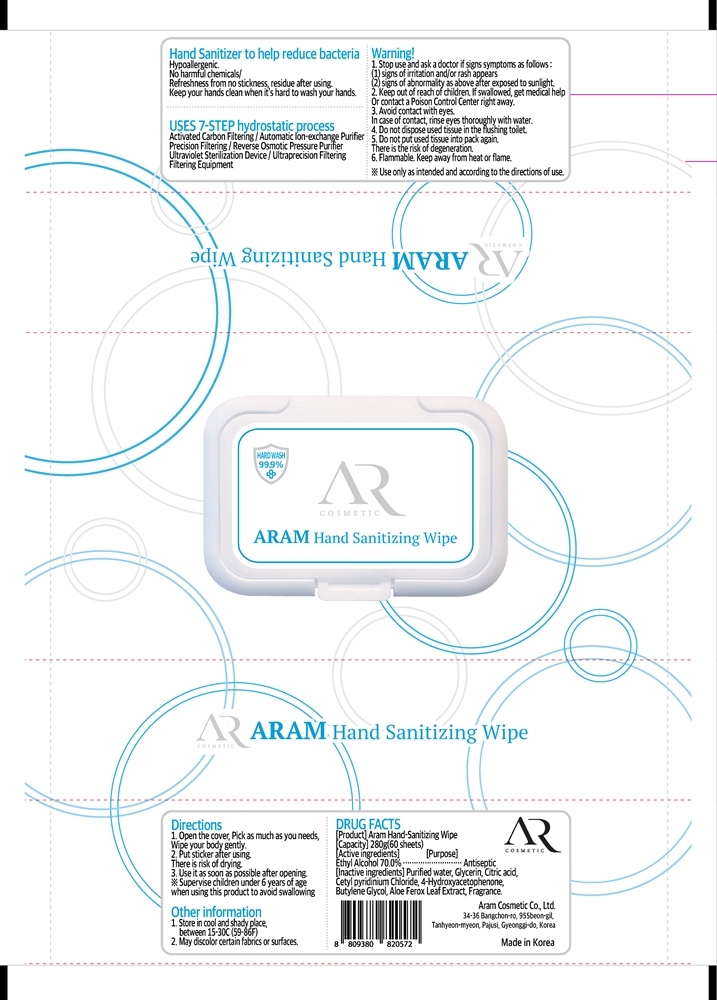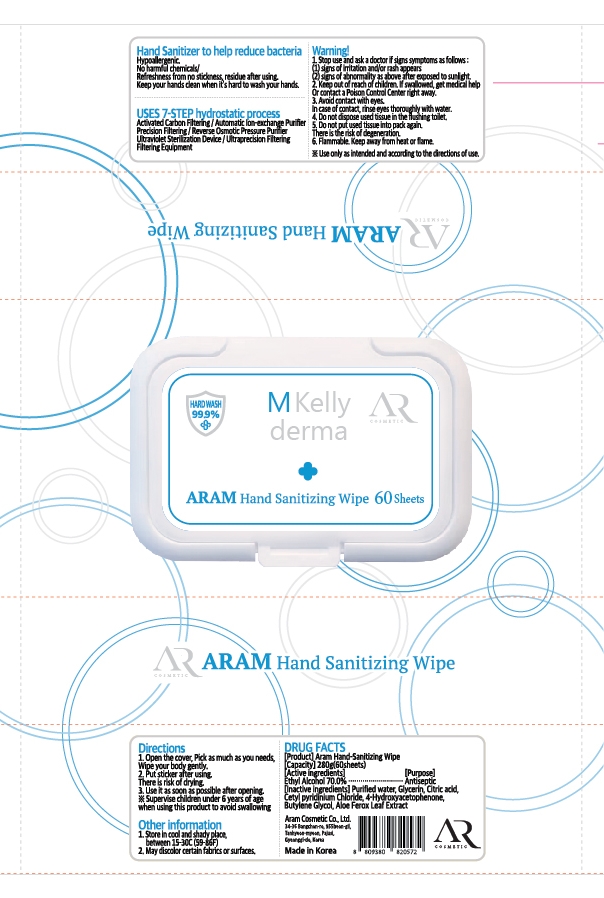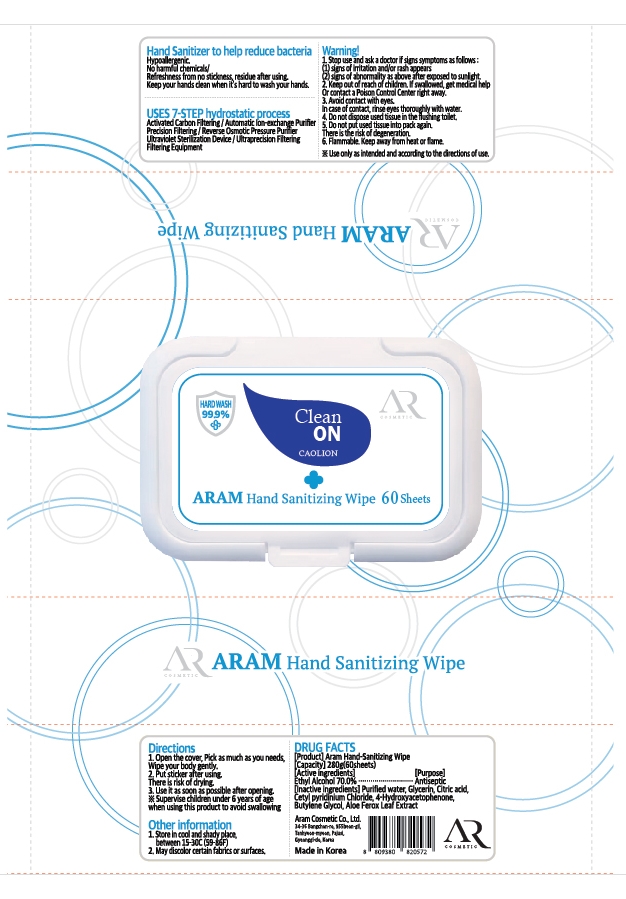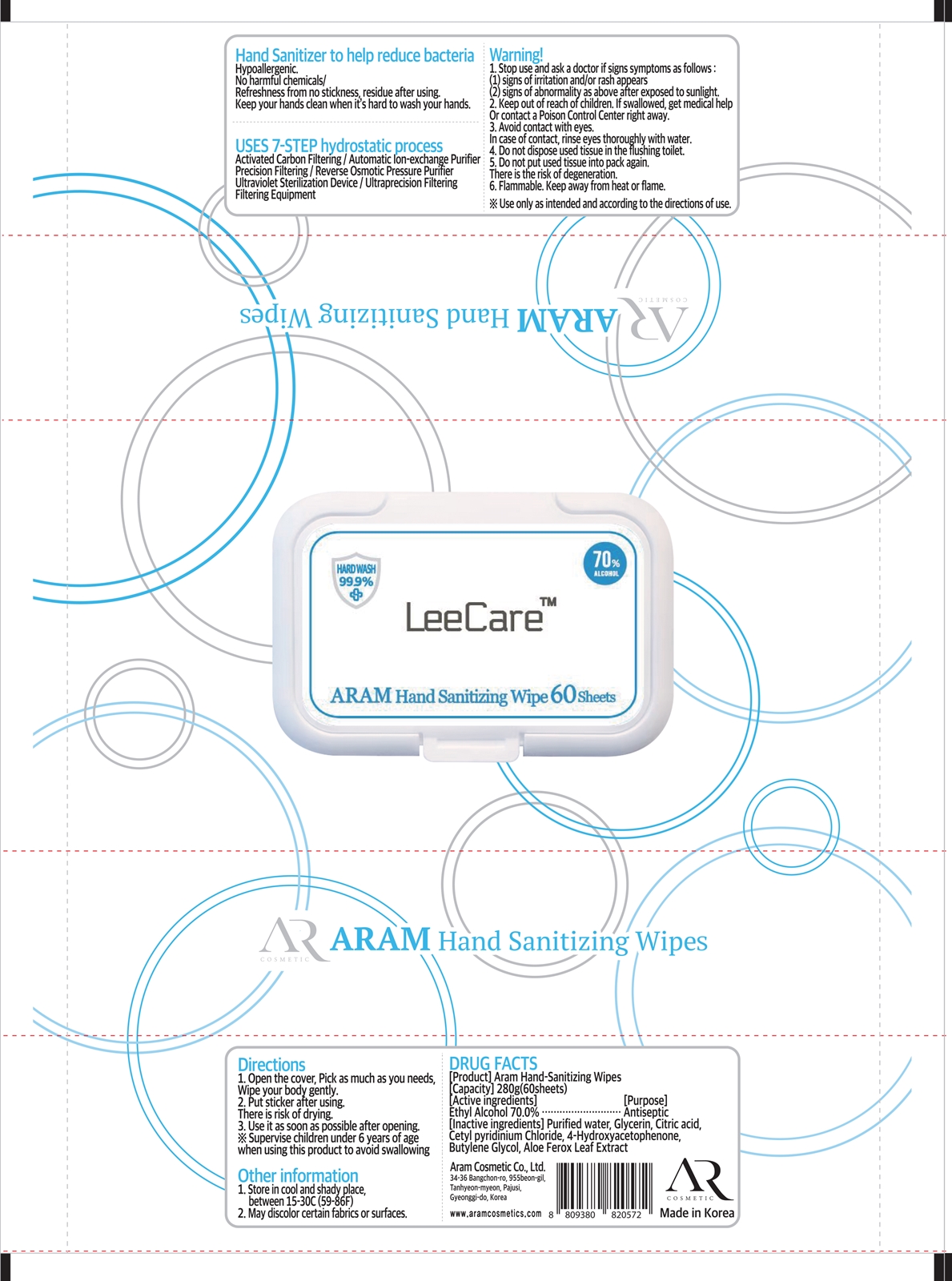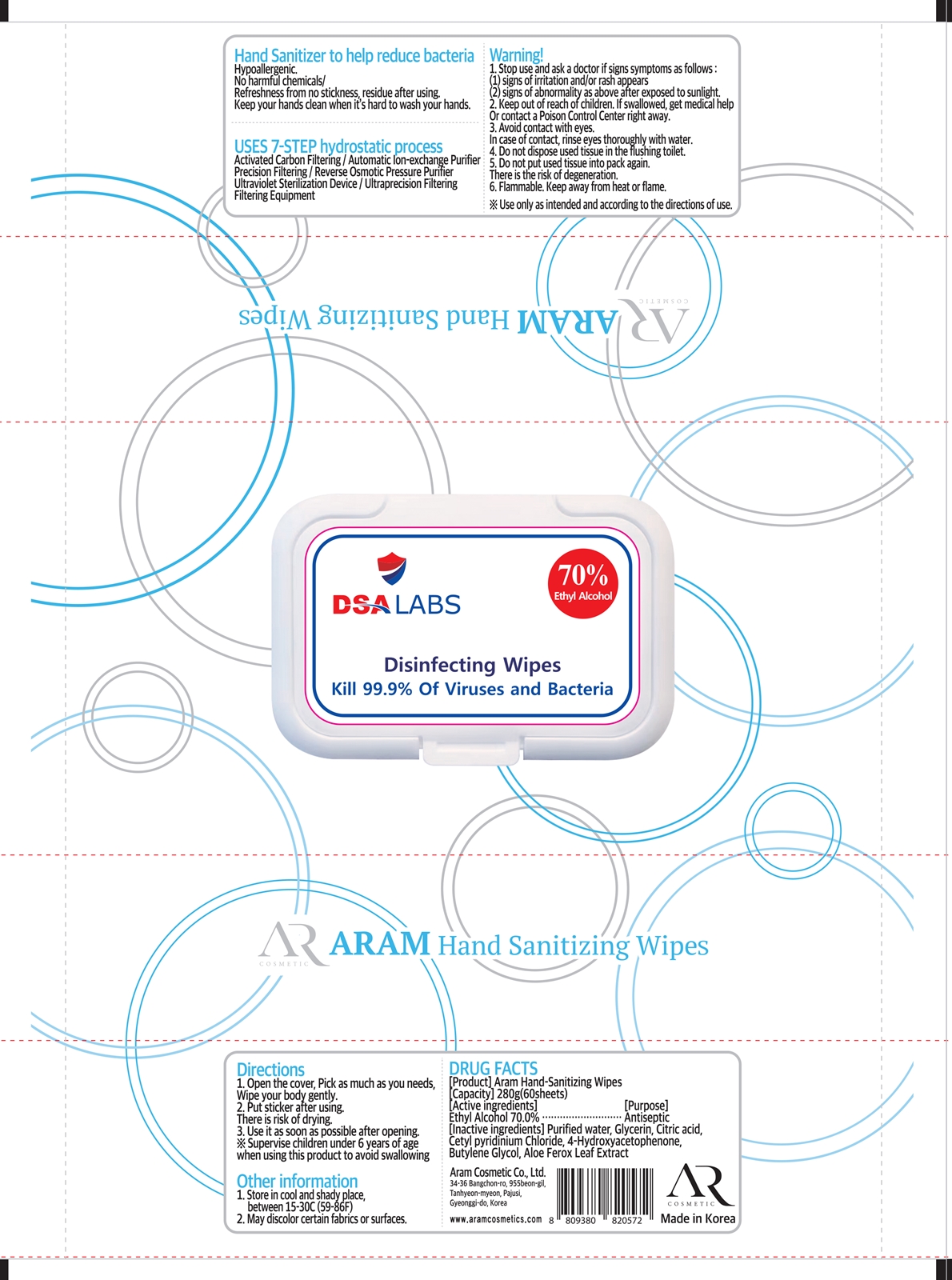 DRUG LABEL: ARAM Hand Sanitizing Wipe
NDC: 75357-201 | Form: LIQUID
Manufacturer: Aram Cosmetic Co., Ltd
Category: otc | Type: HUMAN OTC DRUG LABEL
Date: 20231212

ACTIVE INGREDIENTS: ALCOHOL 70 g/100 g
INACTIVE INGREDIENTS: BUTYLENE GLYCOL 0.02 g/100 g; ALOE FEROX LEAF 0.01 g/100 g; GLYCERIN 1 g/100 g; CETYLPYRIDINIUM CHLORIDE 0.04 g/100 g; CITRIC ACID MONOHYDRATE 0.02 g/100 g; HYDROXYACETOPHENONE 0.08 g/100 g; WATER 28.8 g/100 g

75357-201

Active Ingredient

Ethyl Alcohol 70%

Purpose

Antiseptic

Inactive ingredients

Purified water, Glycerin, Citric acid, Cetyl pyridinium Chloride, 4-Hydroxyacetophenone, Butylene Glycol, Aloe Ferox Leaf Extract

Hand Sanitizer to help reduce bacteria

Hypoallergenic.

No harmful chemicals/

Refreshness from no stickness, residue after using.

Keep your hands clean when it’s hard to wash your hands.

1. Stop use and ask a doctor

if signs symptoms as follows:

(1) signs of irritation and/or rash appears

(2) signs of abnormality as above after exposed to sunlight.

2. Keep out of reach of children.

If swallowed, get medical help

Or contact a Poison Control Center right away.

3. Avoid contact with eyes.

In case of contact, rinse eyes thoroughly with water

Do not dispose used tissue in the flushing toilet.

Do not put used tissue into pack again.

There is the risk of degeneration.

Warning!

6. Flammable. Keep away from heat or flame.

Use only as intended and according to the directions of use.

Directions

1. Open the cover, Pick as much as you needs, Wipe your body gently.

2. Put sticker after using. There is risk of drying.

3. Use it as soon as possible after opening.

※ Supervise children under 6 years of age when using this product to avoid swallowing

Other information

1. Store in cool and shady place, between 15-30C (59-86F)

2. May discolor certain fabrics or surfaces.